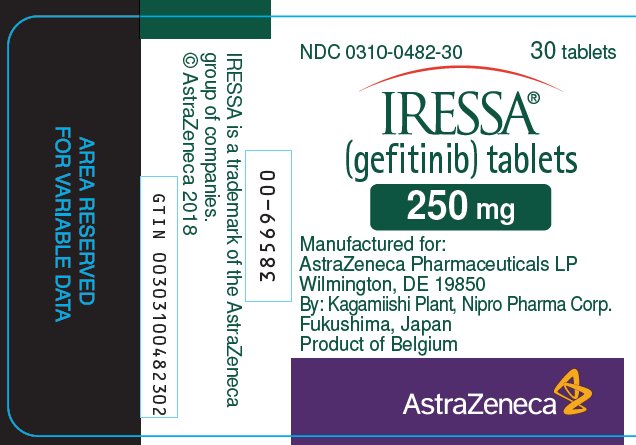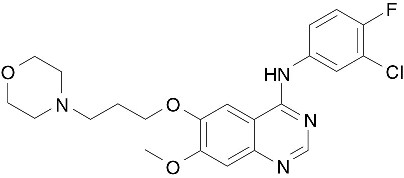 DRUG LABEL: IRESSA
NDC: 0310-0482 | Form: TABLET, COATED
Manufacturer: AstraZeneca Pharmaceuticals LP
Category: prescription | Type: HUMAN PRESCRIPTION DRUG LABEL
Date: 20230228

ACTIVE INGREDIENTS: GEFITINIB 250 mg/1 1
INACTIVE INGREDIENTS: LACTOSE MONOHYDRATE; MICROCRYSTALLINE CELLULOSE; CROSCARMELLOSE SODIUM; POVIDONE, UNSPECIFIED; SODIUM LAURYL SULFATE; MAGNESIUM STEARATE; HYPROMELLOSE, UNSPECIFIED; POLYETHYLENE GLYCOL 300; TITANIUM DIOXIDE; FERRIC OXIDE RED; FERRIC OXIDE YELLOW

HIGHLIGHTS OF PRESCRIBING INFORMATION

These highlights do not include all the information needed to use IRESSA® safely and effectively. See full prescribing information for IRESSA.
IRESSA (gefitinib) tablets for oral use
Initial U.S. Approval: 2015

1 INDICATIONS AND USAGE

IRESSA is a tyrosine kinase inhibitor indicated for the first-line treatment of patients with metastatic non-small cell lung cancer (NSCLC) whose tumors have epidermal growth factor receptor (EGFR) exon 19 deletions or exon 21 (L858R) substitution mutations as detected by an FDA-approved test. (1)

Limitation of Use: Safety and efficacy of IRESSA have not been established in patients whose tumors have EGFR mutations other than exon 19 deletions or exon 21 (L858R) substitution mutations. (1)

2 DOSAGE AND ADMINISTRATION

Recommended dose is 250 mg orally, once daily with or without food. (2.2)

3 DOSAGE FORMS AND STRENGTHS

Tablets: 250 mg. (3)

4 CONTRAINDICATIONS

None. (4)

5 WARNINGS AND PRECAUTIONS

- Interstitial lung disease (ILD): ILD occurred in patients taking IRESSA. Withhold IRESSA for worsening of respiratory symptoms. Discontinue IRESSA if ILD is confirmed. (2.4, 5.1)
- Hepatotoxicity: Obtain periodic liver function testing. Withhold IRESSA for Grade 2 or higher for ALT and/or AST elevations. Discontinue for severe hepatic impairment. (2.4, 5.2)
- Gastrointestinal perforation: Discontinue IRESSA for gastrointestinal perforation. (2.4, 5.3)
- Diarrhea: Withhold IRESSA for Grade 3 or higher diarrhea. (2.4, 5.4)
- Ocular Disorders including Keratitis: Withhold IRESSA for signs and symptoms of severe or worsening ocular disorders including keratitis. Discontinue for persistent ulcerative keratitis. (2.4, 5.5)
- Bullous and Exfoliative Skin Disorders: Withhold IRESSA for Grade 3 or higher skin reactions or exfoliative conditions. (2.4, 5.6)
- Embryo-fetal Toxicity: Can cause fetal harm. Advise of potential risk to a fetus and use of effective contraception. (5.7, 8.1, 8.3)

6 ADVERSE REACTIONS

The most commonly reported adverse drug reactions (ADRs), reported in more than 20% of the patients and greater than placebo were skin reactions and diarrhea. (6.1)

To report SUSPECTED ADVERSE REACTIONS, contact AstraZeneca at 1-800-236-9933 or FDA at 1-800-FDA-1088 or www.fda.gov/medwatch.

7 DRUG INTERACTIONS

- CYP3A4 Inducer: Increase IRESSA to 500 mg daily in patients receiving a strong CYP3A4 inducer. (2.4, 7.1)
- CYP3A4 Inhibitor: Monitor adverse reactions if concomitant use with IRESSA. (7.1)
- Drugs Affecting Gastric pH: Avoid concomitant use of IRESSA with proton pump inhibitors, if possible. (7.1)
- Hemorrhage in patients taking warfarin: Monitor changes in prothrombin time or INR. (7.2)

8 USE IN SPECIFIC POPULATIONS

Lactation: Discontinue breast-feeding. (8.2)

FULL PRESCRIBING INFORMATION

1 INDICATIONS AND USAGE

IRESSA is indicated for the first-line treatment of patients with metastatic non-small cell lung cancer (NSCLC) whose tumors have epidermal growth factor receptor (EGFR) exon 19 deletions or exon 21 (L858R) substitution mutations as detected by an FDA-approved test [see Clinical Studies (14)].

Limitation of Use: Safety and efficacy of IRESSA have not been established in patients with metastatic NSCLC whose tumors have EGFR mutations other than exon 19 deletions or exon 21 (L858R) substitution mutations [see Clinical Studies (14)].

2 DOSAGE AND ADMINISTRATION

2.1 Patient Selection

Select patients for the first-line treatment of metastatic NSCLC with IRESSA based on the presence of EGFR exon 19 deletions or exon 21 L858R mutations in their tumor or plasma specimens [see Indications and Usage (1), Clinical Studies (14)]. If these mutations are not detected in a plasma specimen, test tumor tissue if feasible.

Information on FDA-approved tests for the detection of EGFR mutations in NSCLC is available at: http://www.fda.gov/CompanionDiagnostics.

2.2 Recommended Dose

The recommended dose of IRESSA is 250 mg orally once daily with or without food until disease progression or unacceptable toxicity.

Do not take a missed dose within 12 hours of the next dose.

2.3 Administration to Patients Who Have Difficulty Swallowing Solids

Immerse IRESSA tablets in 4 to 8 ounces of water by dropping the tablet in water, and stir for approximately 15 minutes. Immediately drink the liquid or administer through a naso-gastric tube. Rinse the container with 4 to 8 ounces of water and immediately drink or administer through the naso-gastric tube.

2.4 Dose Modification

Dose Modifications for Adverse Drug Reactions

Withhold IRESSA (for up to 14 days) for any of the following:

- Acute onset or worsening of pulmonary symptoms (dyspnea, cough, fever) [see Warnings and Precautions (5.1)]
- NCI CTCAE Grade 2 or higher in ALT and/or AST elevations [see Warnings and Precautions (5.2)]
- NCI CTCAE Grade 3 or higher diarrhea [see Warnings and Precautions (5.4)]
- Signs and symptoms of severe or worsening ocular disorders including keratitis [see Warnings and Precautions (5.5)]
- NCI CTCAE Grade 3 or higher skin reactions [see Warnings and Precautions (5.6)]

Resume treatment with IRESSA when the adverse reaction fully resolves or improves to NCI CTCAE Grade 1.

Permanently discontinue IRESSA for:

- Confirmed interstitial lung disease (ILD) [see Warnings and Precautions (5.1)]
- Severe hepatic impairment [see Warnings and Precautions (5.2)]
- Gastrointestinal perforation [see Warnings and Precautions (5.3)]
- Persistent ulcerative keratitis [see Warnings and Precautions (5.5)]

Dose Modifications for Drug Interactions

Strong CYP3A4 Inducers

Increase IRESSA to 500 mg daily in the absence of severe adverse drug reaction, and resume IRESSA at 250 mg seven days after discontinuation of the strong CYP3A4 inducer [see Drug Interactions (7), Clinical Pharmacology (12.3)].

3 DOSAGE FORMS AND STRENGTHS

250 mg tablets: round, biconvex, brown film-coated, debossed with "IRESSA 250" on one side and plain on the other side.

4 CONTRAINDICATIONS

None.

5 WARNINGS AND PRECAUTIONS

5.1 Interstitial Lung Disease (ILD)

ILD or ILD-like adverse drug reactions (e.g., lung infiltration, pneumonitis, acute respiratory distress syndrome, or pulmonary fibrosis) occurred in 1.3% of the 2462 patients who received IRESSA across clinical trials; of these, 0.7% were Grade 3 or higher and 3 cases were fatal.

Withhold IRESSA and promptly investigate for ILD in any patient who presents with worsening of respiratory symptoms such as dyspnea, cough and fever. Permanently discontinue IRESSA if ILD is confirmed [see Dosage and Administration (2.4), Adverse Reactions (6.1)].

5.2 Hepatotoxicity

In patients who received IRESSA across clinical trials, 11.4% of patients had increased alanine aminotransferase (ALT), 7.9% of patients had increased aspartate aminotransferase (AST), and 2.7% of patients had increased bilirubin. Grade 3 or higher liver test abnormalities occurred in 5.1% (ALT), 3.0% (AST), and 0.7% (bilirubin) of patients. The incidence of fatal hepatotoxicity was 0.04%.

Obtain periodic liver function testing. Withhold IRESSA in patients with worsening liver function and discontinue in patients with severe hepatic impairment [see Dosage and Administration (2.4), Adverse Reactions (6.1), Use in Specific Populations (8.7)].

5.3 Gastrointestinal Perforation

Gastrointestinal perforation occurred in three (0.1%) of the 2462 IRESSA-treated patients across clinical trials [see Adverse Reactions (6.1)]. Permanently discontinue IRESSA in patients who develop gastrointestinal perforation [see Dosage and Administration (2.4)].

5.4 Severe or Persistent Diarrhea

Grade 3 or 4 diarrhea occurred in 3% of 2462 IRESSA-treated patients across clinical trials. Withhold IRESSA for severe or persistent (up to 14 days) diarrhea [see Dosage and Administration (2.4), Adverse Reactions (6.1)].

5.5 Ocular Disorders including Keratitis

Ocular disorders [keratitis (0.1%), corneal erosion and aberrant eyelash growth (0.2%), conjunctivitis, blepharitis and dry eye (6.7%)] occurred in the 2462 IRESSA-treated patients across clinical trials. The incidence of Grade 3 ocular disorders was 0.1% [see Adverse Reactions (6.1)]. Interrupt or discontinue IRESSA for severe, or worsening ocular disorders [see Dosage and Administration (2.4)].

5.6 Bullous and Exfoliative Skin Disorders

Bullous conditions including toxic epidermal necrolysis, Stevens Johnson syndrome and erythema multiforme have been reported from treatment with IRESSA. Erythema multiforme and dermatitis bullous have been reported in two patients (0.08%) across NSCLC trials (Study 2, Study 3 and Study 4). IRESSA treatment should be interrupted or discontinued if the patient develops severe bullous, blistering or exfoliating conditions.

5.7 Embryo-fetal Toxicity

Based on its mechanism of action and data from animal reproduction studies IRESSA can cause fetal harm when administered to a pregnant woman. In animal reproductive studies, oral administration of gefitinib from organogenesis through weaning resulted in fetotoxicity and neonatal death at doses below the recommended human dose. Advise pregnant women of the potential risk to a fetus. Advise females of reproductive potential to use effective contraception during treatment with IRESSA and for at least two weeks following completion of therapy [see Use in Specific Populations (8.1, 8.3)].

6 ADVERSE REACTIONS

The following adverse drug reactions are discussed in more detail in other sections of the labeling:

- Interstitial Lung Disease [see Warnings and Precautions (5.1)]
- Hepatotoxicity [see Warnings and Precautions (5.2)]
- Gastrointestinal Perforation [see Warnings and Precautions (5.3)]
- Severe or Persistent Diarrhea [see Warnings and Precautions (5.4)]
- Ocular Disorders including Keratitis [see Warnings and Precautions (5.5)]
- Bullous and Exfoliative Skin Disorders [see Warning and Precautions (5.6)]

6.1 Clinical Trials Experience

Because clinical trials are conducted under widely varying conditions, adverse reaction rates observed in the clinical trials of a drug cannot be directly compared to rates in the clinical trials of another drug and may not reflect the rates observed in practice.

The safety of IRESSA is based on the data from 2462 patients with NSCLC who received IRESSA 250 mg daily monotherapy in three randomized clinical studies (Study 2, Study 3 and Study 4). Patients with a history of interstitial lung disease, drug-induced interstitial disease, radiation pneumonitis that required steroid treatment or any evidence of clinically active interstitial lung disease were excluded from these studies.

Controlled Studies:

Study 2 was a randomized, multicenter, open-label trial in which 1217 patients were randomized to receive first-line treatment for metastatic NSCLC; 607 patients received IRESSA 250 mg daily and 589 patients received carboplatin/paclitaxel. The median duration of treatment with IRESSA was 5.9 months. The study population characteristics were: median age 57 years, age less than 65 years (73%), female (79%), Asian (100%), NSCLC adenocarcinoma histology (100%), never smoker (94%), light ex-smoker (6%), ECOG PS 0 or 1 (90%).

Study 3 was a randomized, multicenter, double-blind, placebo-controlled trial in which 1692 patients were randomized to receive second- or third-line treatment for metastatic NSCLC; of which 1126 patients received IRESSA 250 mg daily and 562 patients received placebo. The median duration of treatment with IRESSA was 2.9 months. The study population characteristics were: median age 62 years, age less than 65 years (60%), female (33%), Caucasian (75%), Asian (21%), NSCLC adenocarcinoma histology (48%), never smoker (22%), ECOG PS 0 or 1 (65%), PS 2 (29%), PS 3 (5%) and two or more prior therapies (51%).

Study 4 was a randomized, multicenter, open-label trial in which 1466 patients were randomized to receive second-line treatment for metastatic NSCLC; 729 patients received IRESSA 250 mg daily and 715 patients received docetaxel. The median duration of treatment with IRESSA was 2.4 months. The study population characteristics were: median age 61 years, age less than 65 years (61%), female (36%), Caucasian (79%), Asian (21%), NSCLC adenocarcinoma histology (54%), never smoker (20%), ECOG PS 0 or 1 (88%) and two or more prior therapies (16%).

The pooled safety database from the three randomized trials was used to evaluate for serious and uncommon adverse drug reactions. Common adverse reactions were evaluated in Study 3. The most frequent adverse reactions in Study 3 (incidence of >20% and greater than placebo) reported in IRESSA-treated patients were skin reactions (47%) and diarrhea (29%). The most frequent fatal adverse reactions in IRESSA-treated patients were respiratory failure (0.9%), pneumonia (0.8%), and pulmonary embolism (0.5%).

Approximately 5% of IRESSA-treated patients and 2.3% of placebo-treated patients discontinued treatment due to an adverse event. The most frequent adverse reactions that led to discontinuation in patients treated with IRESSA were nausea (0.5%), vomiting (0.5%) and diarrhea (0.4%).

Table 1 - Selected Adverse Drug Reactions Occurring with an Incidence Rate ≥5% and an Increase of >2% of IRESSA-treated Patients in Study 3
Adverse Reaction | Percentage (%) of patients
Adverse Reaction | IRESSA (N=1126) |  | Placebo (N=562)
Adverse Reaction | All Grades | Grade 3 and 4 | All Grades | Grade 3 and 4
Skin and subcutaneous tissue disorders
Skin reactions [Includes Acne, Acne pustular, Dermatitis, Dermatitis acneiform, Dermatitis exfoliative, Drug eruption, Dry skin, Erythema, Exfoliative rash, Folliculitis, Pruritus, Pruritus generalized, Rash, Rash erythematous, Rash generalized, Rash macular, Rash maculo-papular, Rash papular, Rash pruritic, Rash pustular, Rash vesicular, Skin exfoliation, Skin toxicity, Xeroderma] | 47% | 2% | 17% | 0.4%
Nail disorders [Includes Ingrowing nail, Nail bed infection, Nail disorder, Nail infection, Onychoclasis, Onycholysis, Paronychia] | 5% | 0.1% | 0.7% | 0%
Gastrointestinal disorders
Diarrhea [Includes Diarrhea, Feces soft, Frequent bowel movements] | 29% | 3% | 10% | 1%
Vomiting | 14% | 1.2% | 10% | 0.4%
Stomatitis [Includes Aphthous stomatitis, Cheilitis, Glossodynia, Mouth ulceration, Mucosal inflammation, Oral mucosal blistering, Stomatitis, Tongue disorder, Tongue ulceration] | 7% | 0.3% | 4% | 0.2%
Metabolism and nutrition disorders
Decreased appetite | 17% | 2.3% | 14% | 2.0%
Eye disorders
Conjunctivitis/blepharitis/dry eye [Includes Blepharitis, Conjunctival hyperemia, Conjunctivitis, Dry eye, Eye irritation, Eye pruritus, Eye swelling, Eyelid irritation, Eyelid edema, Eyelids pruritus] | 6% | 0% | 3.2% | 0%

Table 2 - Treatment Emergent Laboratory Abnormalities Occurring More Frequently in IRESSA-Treated Patients in Study 3
Adverse Reaction | IRESSA |  | Placebo
Adverse Reaction | All Grades; % | Grade 3 and 4; % | All Grades; % | Grade 3 and 4; %
Alanine aminotransferase increased [Patients were allowed to enter the clinical study with lab values of ALT or AST CTCAE grade 1 or 2] | 38% [14% gefitinib patients and 10% placebo patients were CTC grade 1 or 2 ALT at baseline] | 2.4% | 23% | 1.4% [0.2% of placebo patients were CTC grade 3 at baseline]
Aspartate aminotransferase increased | 40% [15% gefitinib patients and 12% placebo patients were CTC grade 1 or 2 AST at baseline] | 2.0% | 25% | 1.3% [0.4% of placebo patients were CTC grade 3 at baseline]
Proteinuria | 35% | 4.7% | 31% | 3.3%

The following adverse reactions have been reported with IRESSA across NSCLC trials (Study 2, Study 3 and Study 4) and are not listed elsewhere in Section 6: nausea (18%), asthenia (17%), pyrexia (9%), alopecia (4.7%), hemorrhage (including epistaxis and hematuria) (4.3%), dry mouth (2%), dehydration (1.8%), elevations in blood creatinine (1.5%), allergic reactions including angioedema and urticaria (1.1%), palmar-plantar erythrodysesthesia syndrome (0.2%) and pancreatitis (0.1%).

6.2 Postmarketing Experience

The following adverse reactions have been identified during post-approval use of IRESSA. Because these reactions are reported voluntarily from a population of uncertain size, it is not always possible to reliably estimate their frequency or establish a causal relationship to drug exposure.

Renal and urinary disorders: cystitis, hemorrhagic cystitis

Skin and subcutaneous tissue disorders: cutaneous vasculitis

7 DRUG INTERACTIONS

7.1 Drugs Affecting Gefitinib Exposure

CYP3A4 Inducer

Drugs that are strong inducers of CYP3A4 increase the metabolism of gefitinib and decrease gefitinib plasma concentrations. Increase IRESSA to 500 mg daily in patients receiving a strong CYP3A4 inducer (e.g., rifampicin, phenytoin, or tricyclic antidepressant) and resume IRESSA at 250 mg 7 days after discontinuation of the strong inducer [see Dosage and Administration (2.4), Clinical Pharmacology (12.3)].

CYP3A4 Inhibitor

Drugs that are strong inhibitors of CYP3A4 (e.g., ketoconazole and itraconazole) decrease gefitinib metabolism and increase gefitinib plasma concentrations. Monitor adverse reactions when administering strong CYP3A4 inhibitors with IRESSA.

Drugs Affecting Gastric pH

Drugs that elevate gastric pH (e.g., proton pump inhibitors, histamine H2-receptor antagonists, and antacids) may reduce plasma concentrations of gefitinib. Avoid concomitant use of IRESSA with proton pump inhibitors, if possible. If treatment with a proton-pump inhibitor is required, take IRESSA 12 hours after the last dose or 12 hours before the next dose of the proton-pump inhibitor. Take IRESSA 6 hours after or 6 hours before an H2-receptor antagonist or an antacid [see Clinical Pharmacology (12.3)].

7.2 Hemorrhage in Patients taking Warfarin

International Normalized Ratio (INR) elevations and/or hemorrhage have been reported in some patients taking warfarin while on IRESSA therapy. Patients taking warfarin should be monitored regularly for changes in prothrombin time or INR.

8 USE IN SPECIFIC POPULATIONS

8.1 Pregnancy

Risk Summary

Based on its mechanism of action and animal data, IRESSA can cause fetal harm when administered to a pregnant woman. In animal reproductive studies, oral administration of gefitinib from organogenesis through weaning resulted in fetotoxicity and neonatal death at doses below the recommended human dose (see Animal Data). Advise pregnant women of the potential hazard to a fetus or potential risk for loss of the pregnancy.

The background risk of major birth defects and miscarriage for the indicated population is unknown; however, the background risk in the U.S. general population of major birth defects is 2-4% and miscarriage is 15-20% of clinically recognized pregnancies.

Data

Animal Data

A single dose study in rats showed that gefitinib crosses the placenta after an oral dose of 5 mg/kg (30 mg/m^2, about 0.2 times the recommended human dose on a mg/m^2 basis). When pregnant rats were treated with 5 mg/kg from the beginning of organogenesis to the end of weaning there was a reduction in the number of offspring born alive. This effect was more severe at 20 mg/kg (approximate the human clinical dose on a mg/m^2 basis) and was accompanied by high neonatal mortality soon after parturition. In rabbits, a dose of 20 mg/kg/day (240 mg/m^2, about twice the recommended dose in humans on a mg/m^2 basis) caused reduced fetal weight.

8.2 Lactation

Risk Summary

It is not known whether IRESSA is excreted in human milk. Animal studies indicate the gefitinib and its metabolites are present in rat milk at a concentration higher than those in maternal plasma. Because of the potential for serious adverse reactions in nursing infants from IRESSA, advise women to discontinue breast-feeding during treatment with IRESSA.

Data

Animal Data

Levels of gefitinib and its metabolites were 11-to-19-fold higher in milk than in blood, after oral exposure of lactating rats to a dose of 5 mg/kg.

8.3 Females and Males of Reproductive Potential

Contraception

Based on its mechanism of action and animal data, IRESSA can cause fetal harm when administered to a pregnant woman [see Use in Specific Populations (8.1)]. Advise females of reproductive potential to use effective contraception during treatment with IRESSA and for at least two weeks following completion of therapy.

Infertility

IRESSA may result in reduced fertility in females of reproductive potential [see Nonclinical Toxicology (13.1)].

8.4 Pediatric Use

The safety and effectiveness of IRESSA in pediatric patients have not been established.

8.5 Geriatric Use

Of the 823 patients enrolled in two randomized, active-controlled clinical trials 374 patients (45%) were 65 years and older, and 93 patients (11%) were 75 years and older. No overall differences in safety were observed between patients 65 years and older and those younger than 65 years. There is insufficient information to assess for differences in efficacy between older and younger patients.

8.6 Renal Impairment

Less than four percent (<4%) of gefitinib and its metabolites are excreted via the kidney. No clinical studies were conducted with IRESSA in patients with severe renal impairment.

8.7 Hepatic Impairment

The systemic exposure of gefitinib was compared in patients with mild, moderate, or severe hepatic impairment due to cirrhosis (according to Child-Pugh classification) and healthy subjects with normal hepatic function (N=10/group). The mean systemic exposure (AUC0-∞) was increased by 40% in patients with mild impairment, 263% in patients with moderate impairment, and 166% in patients with severe hepatic impairment. Monitor adverse reactions when IRESSA is administered to patients with moderate and severe hepatic impairment.

In a study comparing 13 patients with liver metastases and moderate hepatic impairment (addition of CTC grade of baseline AST/SGOT, ALP, and bilirubin equals 3 to 5) to 14 patients with liver metastases and normal hepatic function, the systemic exposure of gefitinib was similar [see Warnings and Precautions (5.2)].

10 OVERDOSAGE

Twenty three patients were treated weekly with doses from 1500 mg to 3500 mg, and IRESSA exposure did not increase with increasing dose. Adverse events were mostly mild to moderate in severity, and were consistent with the known safety profile of IRESSA. In the event of suspected overdose, interrupt IRESSA, institute supportive care, and observe until clinical stabilization. There are no specific measures/treatments that should be taken following IRESSA overdosing.

11 DESCRIPTION

Gefitinib is a kinase inhibitor.

The chemical name of gefitinib is 4-Quinazolinamine N-(3-chloro-4-fluorophenyl)-7-methoxy-6-[3-(4-morpholinyl) propoxy] and the following structural formula:

Gefitinib has the molecular formula C22H24ClFN4O3, a relative molecular mass of 446.9 daltons and is a white-colored powder. Gefitinib is a free base. The molecule has pKas of 5.4 and 7.2. Gefitinib can be defined as sparingly soluble at pH 1, but is practically insoluble above pH 7, with the solubility decreasing sharply between pH 4 and pH 6. In non-aqueous solvents, gefitinib is freely soluble in glacial acetic acid and dimethyl sulfoxide, soluble in pyridine, sparingly soluble in tetrahydrofuran, and slightly soluble in methanol, ethanol (99.5%), ethyl acetate, propan-2-ol and acetonitrile.

IRESSA® (gefitinib) tablets are available as brown film-coated tablets, containing 250 mg of gefitinib, for oral administration. The inactive ingredients of the tablet core of IRESSA tablets are lactose monohydrate, microcrystalline cellulose, croscarmellose sodium, povidone, sodium lauryl sulfate and magnesium stearate. The tablet coating is composed of hypromellose, polyethylene glycol 300, titanium dioxide, red ferric oxide and yellow ferric oxide.

12 CLINICAL PHARMACOLOGY

12.1 Mechanism of Action

The epidermal growth factor receptor (EGFR) is expressed on the cell surface of both normal and cancer cells and plays a role in the processes of cell growth and proliferation. Some EGFR activating mutations (exon 19 deletion or exon 21 point mutation L858R) within NSCLC cells have been identified as contributing to the promotion of tumor cell growth, blocking of apoptosis, increasing the production of angiogenic factors and facilitating the processes of metastasis.

Gefitinib reversibly inhibits the kinase activity of wild-type and certain activating mutations of EGFR, preventing autophosphorylation of tyrosine residues associated with the receptor, thereby inhibiting further downstream signaling and blocking EGFR-dependent proliferation.

Gefitinib binding affinity for EGFR exon 19 deletion or exon 21 point mutation L858R mutations is higher than its affinity for the wild-type EGFR. Gefitinib also inhibits IGF and PDGF-mediated signaling at clinically relevant concentrations; inhibition of other tyrosine kinase receptors has not been fully characterized.

12.3 Pharmacokinetics

Absorption and Distribution

The mean oral bioavailability of gefitinib is 60%, with peak plasma levels occurring 3-7 hours after dosing. Food does not alter gefitinib bioavailability to a clinically meaningful extent. IRESSA can be administered with or without food. Gefitinib is extensively distributed throughout the body with a mean steady state volume of distribution of 1400 L following intravenous administration. In vitro binding of gefitinib to human plasma proteins (serum albumin and α1-acid glycoprotein) is 90%, independent of drug concentrations. Gefitinib is a substrate for the membrane transport P-glycoprotein (P-gp), but it is unlikely to influence gefitinib absorption as P-gp is saturated at higher concentrations.

Metabolism and Elimination

Gefitinib undergoes extensive hepatic metabolism in humans, predominantly by CYP3A4. Three sites of biotransformation have been identified: metabolism of the N-propoxymorpholino-group, demethylation of the methoxy-substituent on the quinazoline, and oxidative defluorination of the halogenated phenyl group. Five metabolites have been fully identified in fecal extracts and the major active component was O-desmethyl gefitinib produced by CYP2D6 metabolism and accounted for 14% of the dose.

Eight metabolites were identified in human plasma. Only O-desmethyl gefitinib has exposure comparable to gefitinib. Although this metabolite has similar EGFR-TK activity to gefitinib in the isolated enzyme assay, it had only 1/14 of the potency of gefitinib in one of the cell-based assays.

Gefitinib is cleared primarily by the liver, with total plasma clearance and elimination half-life of 48 hours after intravenous administration. The inter-subject variability (coefficient of variation) for AUC in healthy subjects was 67%. Daily oral administration of gefitinib to cancer patients resulted in a two-fold accumulation compared to single dose administration. Steady state plasma concentrations are achieved within 10 days after daily dosing. Excretion of gefitinib and its metabolites is predominantly via the feces (86%), with renal elimination accounting for less than 4% of the administered dose.

Specific Populations

Age, gender, body weight, ethnicity or renal function: Population pharmacokinetic analyses suggest that patient age, body weight, ethnicity (populations included) or creatinine clearance (above 20 mL/min) has no clinically meaningful effect on predicted steady state trough concentration of gefitinib. Population pharmacokinetic analyses of Study 1 showed that women had 27% higher exposure than men; however, this difference was not identified in the analyses of other gefitinib clinical studies. No dose adjustment based on patient gender is recommended.

Hepatic Impairment: The systemic exposure of gefitinib was compared between patients with mild, moderate, or severe hepatic impairment due to cirrhosis (according to Child-Pugh classification) and healthy subjects with normal hepatic function (N=10/group). The mean systemic exposure (AUC0-∞) was increased by 40% in patients with mild impairment, 263% in patients with moderate impairment, and 166% in patients with severe hepatic impairment. In a study comparing 13 patients with liver metastases and moderate hepatic impairment to 14 patients with liver metastases and normal hepatic function, the systemic exposure of gefitinib was similar [see Warnings and Precautions (5.2), Use in Specific Populations (8.7)].

CYP2D6 Poor metabolizer: CYP2D6 metabolizes gefitinib to O-desmethyl gefitinib in vitro. In healthy CYP2D6 poor metabolizers, O-desmethyl gefitinib concentration was not measurable and the mean exposure to gefitinib was 2-fold higher as compared to the extensive metabolizers. This increase in exposure in CYP2D6 poor metabolizers may be clinically important because some adverse drug reactions are related to higher exposure of gefitinib. No dose adjustment is recommended in patients with a known CYP2D6 poor metabolizer genotype, but these patients should be closely monitored for adverse reactions. The impact of CYP2D6 inhibiting drugs on gefitinib pharmacokinetics has not been evaluated. However, similar precautions should be used when administering CYP2D6 inhibitors with IRESSA because of the possibility of increased exposure in these patients.

An exploratory exposure response analysis showed an increase in the incidence of interstitial lung disease (ILD) with a greater than 2-fold increase in the gefitinib exposure [see Warnings and Precautions (5.1)].

Drug-Drug Interactions

Strong CYP3A4 Inducer:

Concomitant administration of rifampicin (600 mg QD for 16 days), a strong inducer of CYP3A4, with gefitinib (500 mg single dose on Day 10 of gefitinib administration) reduced mean AUC of gefitinib by 83% [see Dosage and Administration (2.4), Drug Interactions (7)].

CYP3A4 Inhibitor:

Concomitant administration of itraconazole (200 mg QD for 12 days), an inhibitor of CYP3A4, with gefitinib (250 mg single dose on Day 4 of itraconazole administration) to healthy male subjects, increased mean gefitinib AUC by 80% [see Drug Interactions (7)].

Drugs Affecting Gastric pH:

Co-administration of high doses of ranitidine with sodium bicarbonate (to maintain the gastric pH above pH 5.0) to healthy subjects decreased mean gefitinib AUC by 47% [see Drug Interactions (7)].

In human liver microsome studies, gefitinib had no inhibitory effect on CYP1A2, CYP2C9, and CYP3A4 activities at concentrations ranging from 2-5000 ng/mL. At the highest concentration studied (5000 ng/mL), gefitinib inhibited CYP2C19 by 24% and CYP2D6 by 43%.

Exposure to metoprolol, a substrate of CYP2D6, was increased by 30% when it was given on Day 15 of gefitinib dosing (500 mg daily for 28 days) in patients with solid tumors.

13 NONCLINICAL TOXICOLOGY

13.1 Carcinogenesis, Mutagenesis, Impairment of Fertility

Gefitinib has been tested for genotoxicity in a series of in vitro (bacterial mutation, mouse lymphoma, and human lymphocyte) assays and an in vivo rat micronucleus test. Under the conditions of these assays, gefitinib did not cause genetic damage.

In a two-year carcinogenicity study in mice, administration of gefitinib at a dose of 270 mg/m^2/day (approximately twice the recommended daily dose of 250 mg on a mg/m^2 basis; dose reduced from 375 mg/m^2/day from week 22) caused hepatocellular adenomas in females. In a two-year carcinogenicity study in rats, administration of gefitinib at 60 mg/m^2/day (approximately 0.4 times the recommended daily clinical dose on a mg/m^2 basis) caused hepatocellular adenomas and hemangiomas/hemagiosarcomas of the mesenteric lymph nodes in female rats. The clinical relevance of these findings is unknown.

In a dedicated fertility study in rats at doses ≥120 mg/m^2 (approximately equal to the recommended human dose of gefitinib on a mg/m^2 basis), animals presented with an increased incidence of irregular estrous, decreased corpora lutea, and decreases in uterine implants and live embryos per litter.

14 CLINICAL STUDIES

Non-Small Cell Lung Cancer (NSCLC)

Study 1

The efficacy and safety of IRESSA for the first-line treatment of patients with metastatic NSCLC containing EGFR exon 19 deletions or L858R substitution mutations was demonstrated in a multicenter, single-arm, open-label clinical study (Study 1). A total of 106 treatment-naive patients with metastatic EGFR mutation positive NSCLC received IRESSA at a dose of 250 mg once daily until disease progression or intolerable toxicity. The major efficacy outcome measure was objective response rate (ORR) according to RECIST v1.1 as evaluated by both a Blinded Independent Central Review (BICR) and investigators. Duration of response (DOR) was an additional outcome measure. Eligible patients were required to have a deletion in EGFR exon 19 or L858R, L861Q, or G719X substitution mutation and no T790M or S768I mutation or exon 20 insertion in tumor specimens as prospectively determined by a clinical trial assay. Tumor samples from 87 patients were tested retrospectively using the therascreen® EGFR RGQ PCR Kit.

The study population characteristics were: median age 65 years, age 75 years or older (25%), age less than 65 years (49%), white (100%), female (71%), never smokers (64%), WHO PS 0 (45%), WHO PS 1 (48%), WHO PS 2 (7%), and adenocarcinoma histology (97%). Sixty patients had exon 19 deletions (65%), 29 patients had L858R substitution (31%), while two patients each had tumors harboring L861Q or G719X substitution mutation.

The median duration of treatment was 8.0 months. Efficacy results from Study 1 are summarized below.

Table 3 – Efficacy Results in Study 1
Efficacy Parameter | BICR [BICR, Blinded Independent Central Review] Assessment; (n=106) [17 patients without target lesion at baseline detected by BICR were deemed non responders] | Investigator Assessment (n=106)
Objective Response Rate [Determined by RECIST v 1.1]; (95% CI) | 50%; (41, 59) | 70%; (61, 78)
Complete Response Rate | 0.9% | 1.9%
Partial Response Rate | 49% | 68%
Median Duration of Response (months); (95% CI) | 6.0; (5.6, 11.1) | 8.3; (7.6, 11.3)

The response rates were similar in patients whose tumors had EGFR exon 19 deletions and exon 21 L858R substitution mutations. Two partial responses were observed in both patients whose tumors had G719X substitution mutation with duration of response of at least 2.8 months and 5.6 months, respectively. One of two patients whose tumors had L861Q substitution mutation also achieved a partial response with duration of response of at least 2.8 months.

Study 2

The results of Study 1 were supported by an exploratory analysis of a subset of a randomized, multicenter, open-label trial (Study 2) conducted in patients with metastatic adenocarcinoma histology NSCLC receiving first-line treatment. Patients were randomized (1:1) to receive IRESSA 250 mg orally once daily or up to 6 cycles of carboplatin/paclitaxel. The efficacy outcomes included progression-free survival (PFS) and objective response rate (ORR) as assessed by BICR.

The subset population consisted of 186 of 1217 patients (15%) determined to be EGFR positive by the same clinical trial assay as used in Study 1 and had radiographic scans available for a retrospective assessment by BICR. In this subset, there were 88 IRESSA-treated patients and 98 carboplatin/paclitaxel-treated patients.

Demographic and baseline characteristics of this subset were a median age of 59 years, age 75 years or older (7%), age less than 65 (70%), Asian (100%), female (83%), never smokers (96%), adenocarcinoma histology (100%), and PS 0-1 (94%).

The median duration of treatment for IRESSA-treated patients was 9.8 months. The hazard ratio for PFS favored the IRESSA-treated patients [HR of 0.54 (95% CI: 0.38, 0.79)] with a median PFS of 10.9 months for the IRESSA-treated patients and 7.4 months for the carboplatin/paclitaxel-treated patients as assessed by BICR. In addition, the objective response rate was 67% (95% CI: 56, 77) for IRESSA-treated patients and 41% (95% CI: 31, 51) for carboplatin/paclitaxel-treated patients based on BICR assessment. The median duration of response was 9.6 months for IRESSA-treated patients and 5.5 months for carboplatin/paclitaxel-treated patients.

16 HOW SUPPLIED/STORAGE AND HANDLING

IRESSA® (gefitinib) is available as 250 mg tablets.

IRESSA 250 mg tablets are round, biconvex, brown film-coated, debossed with "IRESSA 250" on one side and plain on the other side.

IRESSA® (gefitinib) tablets are supplied as:

Bottles of 30 Tablets (NDC 0310-0482-30)

Store at controlled room temperature 20°C-25°C (68°F-77°F) [see USP Controlled Room Temperature].

17 PATIENT COUNSELING INFORMATION

Advise the patient to read the FDA-approved patient labelling (Patient Information).

Interstitial Lung Disease: Advise patients to immediately contact their healthcare provider for new onset or worsening of pulmonary symptoms such as dyspnea, cough and fever [see Warnings and Precautions (5.1)].

Hepatotoxicity: Inform patients that they will need to undergo lab tests to monitor for liver function. Advise patients to contact their healthcare provider to report any new symptoms indicating hepatic toxicity [see Warnings and Precautions (5.2)].

Gastrointestinal Perforation: Advise patients that IRESSA can increase the risk of gastrointestinal perforation and to seek immediate medical attention for severe abdominal pain [see Warnings and Precautions (5.3)].

Severe or Persistent Diarrhea: Advise patients to contact their healthcare provider for severe or persistent diarrhea [see Warnings and Precautions (5.4)].

Ocular Disorders including Keratitis: Advise patients promptly to contact their healthcare provider if they develop eye symptoms, lacrimation, light sensitivity, blurred vision, eye pain, red eye or changes in vision [see Warnings and Precautions (5.5)].

Bullous and Exfoliative Skin Disorders: Advise patients that IRESSA can increase the risk of bullous and exfoliative skin disorders and to seek immediately medical attention for severe skin reactions [see Warnings and Precautions (5.6)].

Embryo-fetal Toxicity: Advise pregnant women of the potential risk to a fetus or potential risk for loss of the pregnancy [see Warnings and Precautions (5.7), Use in Specific Populations (8.1)]. Advise females of reproductive potential to use effective contraception during treatment with IRESSA and for at least two weeks following completion of therapy [see Use in Specific Populations (8.3)].

Lactation: Advise women to discontinue breast-feeding during treatment with IRESSA [see Use in Specific Populations (8.2)].

IRESSA is a trademark of the AstraZeneca group of companies.

©AstraZeneca 2023

Distributed by:

AstraZeneca Pharmaceuticals LP

Wilmington, DE 19850

Patient Information

IRESSA (eye-RES-sah)

(gefitinib) tablets

What is IRESSA?

IRESSA is a prescription medicine used to treat people with non-small cell lung cancer (NSCLC) that has spread to other parts of the body and:

- that have certain types of abnormal epidermal growth factor receptor (EGFR) genes, and
- who have not had previous treatment for cancer

Your healthcare provider will perform a test to make sure that IRESSA is right for you.

It is not known if IRESSA is safe and effective in people with NSCLC that have other types of EGFR genes.

It is not known if IRESSA is safe and effective in children.

Before taking IRESSA, tell your healthcare provider about all of your medical conditions, including if you:

- have lung or breathing problems
- ever had liver problems
- have vision or eye problems
- are pregnant or plan to become pregnant. IRESSA can harm your unborn baby.
  ∘ Females who are able to become pregnant should use an effective method of birth control during treatment with IRESSA and for at least 2 weeks after the last dose of IRESSA. You should avoid becoming pregnant during treatment with IRESSA.
  ∘ Tell your healthcare provider right away if you become pregnant during treatment with IRESSA.
- are breastfeeding or plan to breastfeed. It is not known if IRESSA passes into your breast milk. Do not breastfeed during treatment with IRESSA. Talk to your healthcare provider about the best way to feed your baby during this time.

Tell your healthcare provider about all the medicines you take, including prescription and over-the-counter medicines, vitamins, or herbal supplements.

If you take a proton pump inhibitor (PPI), H2 blocker, or an antacid medicine, talk to your healthcare provider about the best time to take it during treatment with IRESSA.

If you take a blood thinner called warfarin, your healthcare provider should do blood tests regularly to check how fast your blood clots, during treatment with IRESSA.

How should I take IRESSA?

- Take IRESSA exactly as your healthcare provider tells you to take it.
- Your healthcare provider may change your dose, temporarily stop, or permanently stop treatment with IRESSA if you have side effects.
- Take IRESSA 1 time each day.
- You can take IRESSA with or without food.
- If you miss a dose of IRESSA, take it as soon as you remember. If it is less than 12 hours until your next dose, skip the missed dose. Take your next dose at your regular time.
- If you take too much IRESSA, call your healthcare provider or go to the nearest emergency room right away.
- If you cannot swallow IRESSA tablets whole:
  ∘ place your dose of IRESSA in a container with 4 to 8 ounces of water and stir for about 15 minutes
  ∘ drink the mixture right away
  ∘ place another 4 to 8 ounces of water in the same container, and drink it right away

What are the possible side effects of IRESSA?

IRESSA may cause serious side effects, including:

- lung or breathing problems. IRESSA may cause inflammation of the lung that may lead to death. Symptoms may be similar to those symptoms from lung cancer. Tell your healthcare provider right away if you have any new or worsening lung problems, or any combination of the following symptoms: trouble breathing or shortness of breath, cough, or fever.
- liver problems. IRESSA may cause inflammation of the liver that may lead to death. Tell your healthcare provider right away if you have any symptoms of a liver problem which may include:
  ∘ yellowing of your skin or the white part of your eyes (jaundice)
  ∘ dark or brown (tea colored) urine
  ∘ light-colored bowel movements (stools)
  ∘ decreased appetite
  ∘ pain on the right side of your stomach (abdomen)

Your healthcare provider will do blood tests to check your liver function during your treatment with IRESSA.

- a tear in the wall of your stomach or intestines (perforation). Get emergency medical help right away if you have severe stomach (abdomen) pain.
- diarrhea. Diarrhea is common with IRESSA and can sometimes be severe. Tell your healthcare provider right away if you have severe diarrhea or diarrhea that will not go away.
- eye problems. Tell your healthcare provider if you get watery eyes, sensitivity to light, blurred vision, eye pain, eye redness, or vision changes.
- skin reactions. Skin redness, rash, itching, and acne are common with IRESSA. This may occur on any part of your body. Get medical help right away if you develop severe skin reactions such as peeling or blistering of your skin.

IRESSA may cause fertility problems in females. Talk to your healthcare provider if you plan to become pregnant.

Tell your healthcare provider if you have any side effect that bothers you or that does not go away.

These are not all the possible side effects of IRESSA. For more information, ask your healthcare provider or pharmacist.

Call your doctor for medical advice about side effects.

You may report side effects to FDA at 1-800-FDA-1088.

How should I store IRESSA?

Store IRESSA at room temperature between 68˚F to 77˚F (20˚C to 25˚C)

Keep IRESSA and all medicines out of the reach of children.

General information about the safe and effective use of IRESSA.

Medicines are sometimes prescribed for purposes other than those listed in Patient Information leaflet. Do not use IRESSA for a condition for which it was not prescribed. Do not give IRESSA to other people, even if they have the same symptoms you have. It may harm them. You can ask your healthcare provider or pharmacist for information about IRESSA that is written for health professionals.

What are the ingredients in IRESSA?

Active ingredient: gefitinib

Inactive ingredients: lactose monohydrate, microcrystalline cellulose, croscarmellose sodium, povidone, sodium lauryl sulfate, magnesium stearate

Tablet coating contains: hypromellose, polyethylene glycol 300, titanium dioxide, yellow iron oxide and red iron oxide.

IRESSA is a trademark of the AstraZeneca group of companies.

©AstraZeneca 2021

Distributed by:

AstraZeneca Pharmaceuticals LP

Wilmington, DE 19850

For more information, go to www.iressa.com or call 1-800-236-9933

This Patient Information has been approved by the U.S. Food and Drug Administration. Issued: May 2021

PACKAGE/LABEL PRINCIPAL DISPLAY PANEL – 250 mg

NDC 0310-0482-30 30 tablets

IRESSA®

(gefitinib) tablets

250 mg

Manufactured for:

AstraZeneca Pharmaceuticals LP

Wilmington, DE 19850

By: Kagamiishi Plant, Nipro Pharma Corp.

Fukushima, Japan

Product of Belgium

AstraZeneca